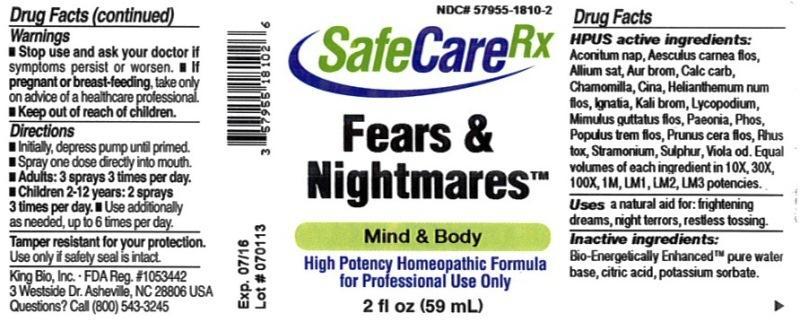 DRUG LABEL: Fears and Nightmares
NDC: 57955-1810 | Form: LIQUID
Manufacturer: King Bio Inc.
Category: homeopathic | Type: HUMAN OTC DRUG LABEL
Date: 20130813

ACTIVE INGREDIENTS: ACONITUM NAPELLUS 10 [hp_X]/59 mL; AESCULUS CARNEA FLOWER 10 [hp_X]/59 mL; GARLIC 10 [hp_X]/59 mL; GOLD TRIBROMIDE 10 [hp_X]/59 mL; OYSTER SHELL CALCIUM CARBONATE, CRUDE 10 [hp_X]/59 mL; MATRICARIA RECUTITA 10 [hp_X]/59 mL; ARTEMISIA CINA PRE-FLOWERING TOP 10 [hp_X]/59 mL; HELIANTHEMUM NUMMULARIUM FLOWER 10 [hp_X]/59 mL; STRYCHNOS IGNATII SEED 10 [hp_X]/59 mL; POTASSIUM BROMIDE 10 [hp_X]/59 mL; LYCOPODIUM CLAVATUM SPORE 10 [hp_X]/59 mL; MIMULUS GUTTATUS FLOWERING TOP 10 [hp_X]/59 mL; PAEONIA OFFICINALIS ROOT 10 [hp_X]/59 mL; PHOSPHORUS 10 [hp_X]/59 mL; POPULUS TREMULA FLOWERING TOP 10 [hp_X]/59 mL; TOXICODENDRON PUBESCENS LEAF 10 [hp_X]/59 mL; DATURA STRAMONIUM 10 [hp_X]/59 mL; SULFUR 10 [hp_X]/59 mL; VIOLA ODORATA 10 [hp_X]/59 mL
INACTIVE INGREDIENTS: WATER; CITRIC ACID MONOHYDRATE; POTASSIUM SORBATE

Fears & Nightmares™

Drug Facts

____________________________________________________________________________________________________________

HPUS active ingredients Aconitum napellus, Aesculus carnea, flos, Allium sativum, Aurum bromatum, Calcarea carbonica, Chamomilla, Cina, Helianthemum nummularium, flos, Ignatia amara, Kali bromatum, Lycopodium clavatum, Mimulus guttatus, flos, Paeonia officinalis, Phosphorus, Populus tremula, flos, Rhus toxicodendron, Stramonium, Sulphur, Viola odorata. Equal volumes of each ingredient in 10X, 30X, 100X, 1M, LM1, LM2, LM3 potencies.

INDICATIONS AND USAGE

Uses a natural aid for: frightening dreams, night terrors, restless tossing.

INACTIVE INGREDIENT

Inactive ingredients: Bio-Energetically Enhanced pure water base, citric acid, potassium sorbate.

Warnings

- Stop use and ask your doctor if symptoms persist or worsen.
- If pregnant or breast-feeding, take only on advice of a healthcare professional.

- Keep out of reach of children.

Directions:

- Initially, depress pump until primed.
- Spray one dose directly into mouth.
- Adults: 3 sprays 3 times per day.
- Children 2-12 years: 2 sprays 3 times per day.
- Use additionally as needed, up to 6 times per day.

OTHER SAFETY INFORMATION

Tamper resistant for your protection. Use only if safety seal is intact.

PURPOSE

Uses a natural aid for: frightening dreams, night terrors, restless tossing.